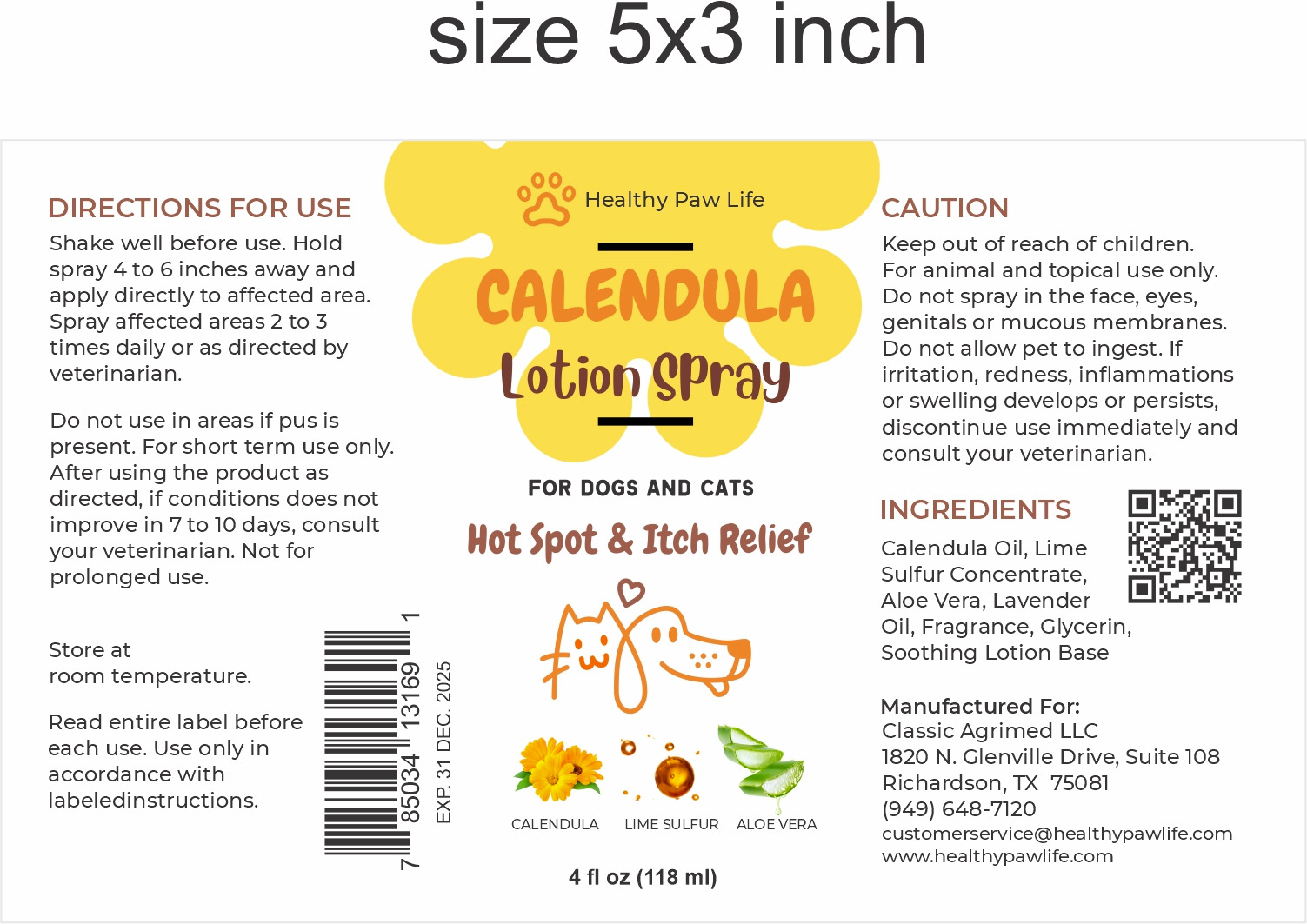 DRUG LABEL: CALENDULA SP
NDC: 86130-201 | Form: LIQUID
Manufacturer: CLASSIC AGRIMED LLC
Category: animal | Type: OTC ANIMAL DRUG LABEL
Date: 20231108

ACTIVE INGREDIENTS: CALENDULA OFFICINALIS SEED OIL 1 g/100 mL; CALCIUM POLYSULFIDE 0.7 g/100 mL
INACTIVE INGREDIENTS: aloe; WATER; COCONUT OIL; LAVENDER OIL

Calendula Lotion

Ingredients: Calendula Oil, Lime Sulfur Concentrate, Aloe Vera, Lavender Oil, Fragrance, Glycerin, Soothing Lotion Base

Directions For Use: Shake well before use. Hold spray 4 to 6 inches away and apply directly to affected area. Spray affected areas 2 to 3 times daily or as directed by veterinarian.

Do not use in areas if pus is present. For short term use only. After using the product as directed, if conditions does not improve in 7 to 10 days, consult your veterinarian. Not for prolonged use.

Store at room temperature.

Read entire label before each use. Use only in accordance with labeled instructions.

Caution:

Keep out of reach of children.
For animal and topical use only. Do not spray in the face, eyes, genitals or mucous membranes. Do not allow pet to ingest. If irritation, redness, inflammations or swelling develops or persists, discontinue use immediately and consult your veterinarian.